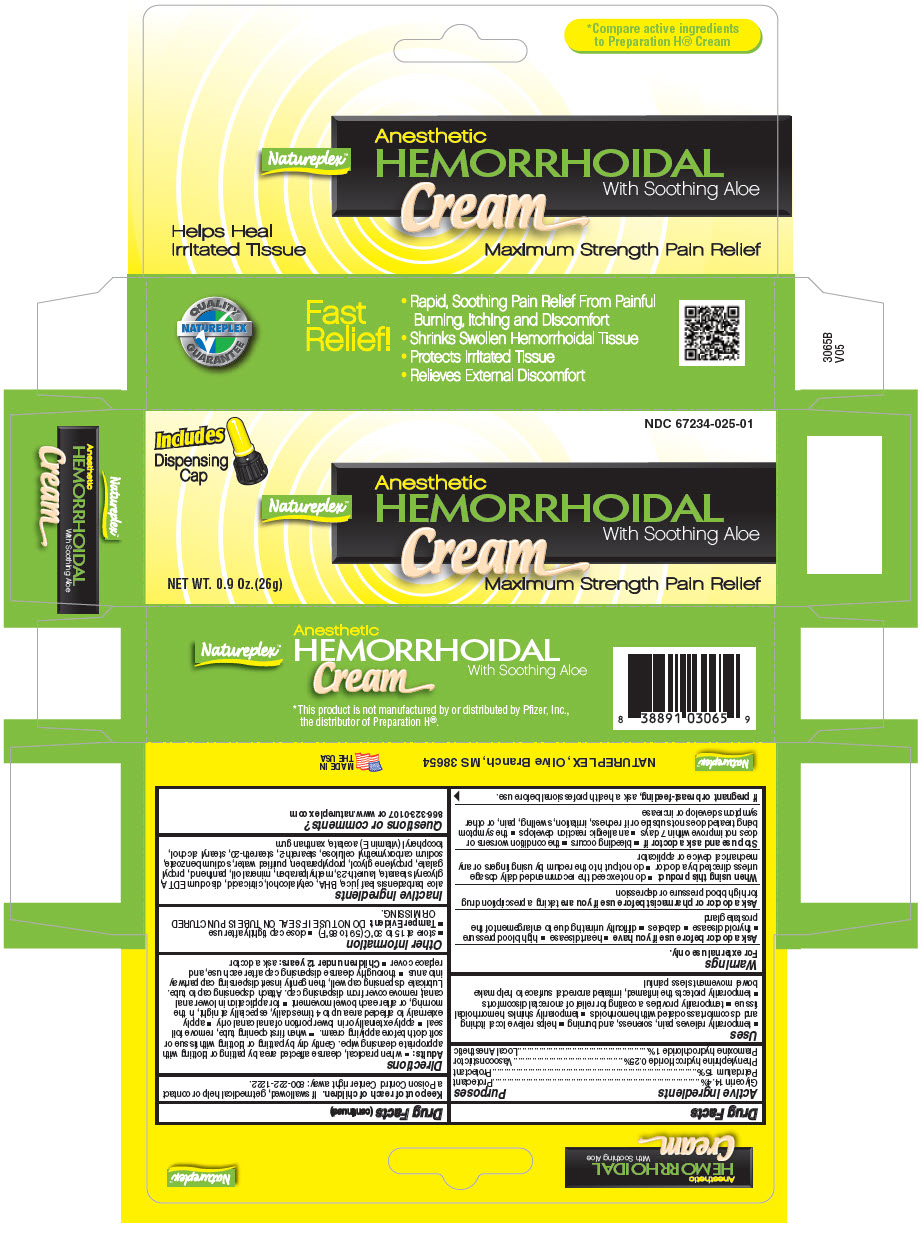 DRUG LABEL: Natureplex 
NDC: 67234-025 | Form: CREAM
Manufacturer: Natureplex LLC
Category: otc | Type: HUMAN OTC DRUG LABEL
Date: 20241231

ACTIVE INGREDIENTS: GLYCERIN 0.144 mg/1 g; PHENYLEPHRINE HYDROCHLORIDE 0.0025 mg/1 g; PRAMOXINE HYDROCHLORIDE 0.1 mg/1 g; PETROLATUM 0.15 mg/1 g
INACTIVE INGREDIENTS: ALOE VERA LEAF; BUTYLATED HYDROXYANISOLE; CARBOXYMETHYLCELLULOSE SODIUM, UNSPECIFIED; CETOSTEARYL ALCOHOL; CITRIC ACID MONOHYDRATE; EDETATE DISODIUM; GLYCERYL MONOSTEARATE; LAURETH-23; METHYLPARABEN; MINERAL OIL; PANTHENOL; PROPYL GALLATE; PROPYLENE GLYCOL; PROPYLPARABEN; SODIUM BENZOATE; STEARETH-2; STEARETH-20; STEARYL ALCOHOL; TOCOPHEROL; .ALPHA.-TOCOPHEROL; WATER; XANTHAN GUM

Natureplex™
Hemorrhoidal

Drug Facts

ACTIVE INGREDIENT

PURPOSE

Active ingredients | Purposes
Glycerin 14.4% | Protectant
Petrolatum 15% | Protectant
Phenylephrine hydrochloride 0.25% | Vasoconstrictor
Pramoxine hydrochloride 1% | Local Anesthetic

Uses

- temporarily relieves pain, soreness, and burning
- helps relieve local itching and discomfort associated with hemorrhoids
- temporarily shrinks hemorrhoidal tissue
- temporarily provides a coating for relief of anorectal discomforts
- temporarily protects the inflamed, irritated anorectal surface to help make bowel movements less painful

Warnings

For external use only.

Ask a doctor before use if you have

- heart disease
- high blood pressure
- thyroid disease
- diabetes
- difficulty urinating due to enlargement of the prostate gland

Ask a doctor or pharmacist before use if you are taking a prescription drug for high blood pressure or depression

When using this product

- do not exceed the recommended daily dosage unless directed by a doctor
- do not put into the rectum by using fingers or any mechanical device or applicator

Stop use and ask a doctor if

- bleeding occurs
- the condition worsens or does not improve within 7 days
- an allergic reaction develops
- the symptom being treated does not subside or if redness, irritation, swelling, pain, or other symptoms develop or increase

PREGNANCY OR BREAST FEEDING

If pregnant or breast-feeding, ask a health professional before use.

Keep out of reach of children. If swallowed, get medical help or contact a Poison Control Center right away: 800-222-1222.

Directions

Adults:

- when practical, cleanse affected area by patting or blotting with appropriate cleansing wipe. Gently dry by patting or blotting with tissue or soft cloth before applying cream.
- when first opening tube, remove foil seal
- apply externally or in lower portion of anal canal only
- apply externally to affected area up to 4 times daily, especially at night, in the morning, or after each bowel movement
- for application in lower anal canal; remove cover from dispensing cap. Attach dispensing cap to tube. Lubricate dispensing cap well, then gently insert dispensing cap partway into anus
- thoroughly cleanse dispensing cap after each use, and replace cover
- Children under 12 years: ask a doctor

Other information

- store at 15 to 30°C (59 to 86°F)
- close cap tightly after use
- Tamper Evident: DO NOT USE IF SEAL ON TUBE IS PUNCTURED OR MISSING.

Inactive ingredients

aloe barbadensis leaf juice, BHA, cetyl alcohol, citric acid, disodium EDTA, glyceryl stearate, laureth-23, methylparaben, mineral oil, panthenol, propyl gallate, propylene glycol, propylparaben, purified water, sodium benzoate, sodium carboxymethyl cellulose, steareth-2, steareth-20, stearyl alcohol, tocopheryl (vitamin E) acetate, xanthan gum

Questions or comments?

866-323-0107 or www.natureplex.com

PRINCIPAL DISPLAY PANEL - 26 g Tube Box

NDC 67234-025-01

Includes
Dispensing
Cap

Natureplex™

Anesthetic
HEMORRHOIDAL
Cream
With Soothing Aloe

NET WT. 0.9 Oz.(26g)
Maximum Strength Pain Relief